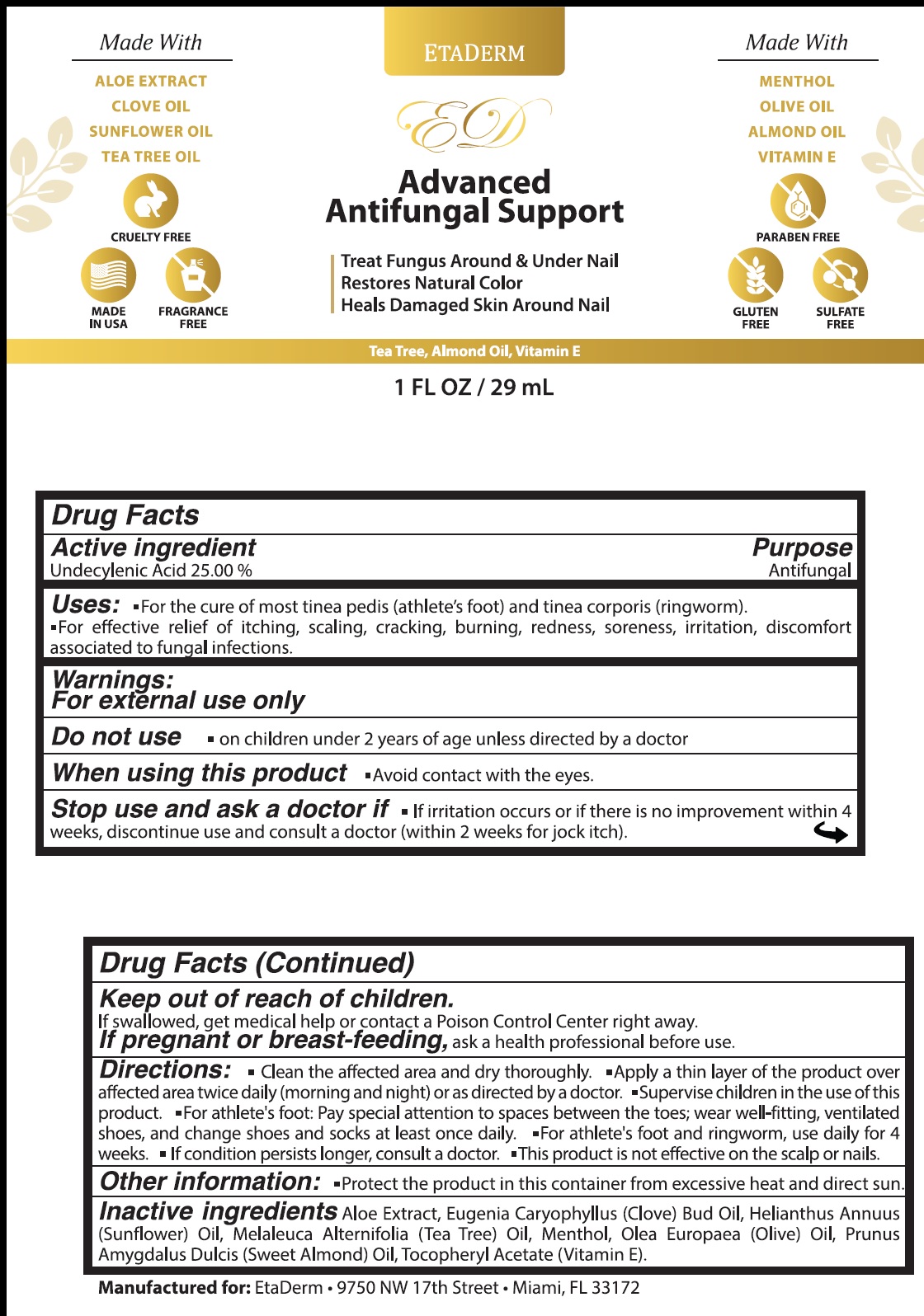 DRUG LABEL: ETADERM Advanced Antifungal Support
NDC: 84180-471 | Form: CREAM
Manufacturer: NUEPHASE LLC
Category: otc | Type: HUMAN OTC DRUG LABEL
Date: 20240313

ACTIVE INGREDIENTS: UNDECYLENIC ACID 250 mg/1 mL
INACTIVE INGREDIENTS: ALOE; CLOVE OIL; SUNFLOWER OIL; TEA TREE OIL; MENTHOL; OLIVE OIL; ALMOND OIL; .ALPHA.-TOCOPHEROL ACETATE

ETADERM Advanced Antifungal Support

Active ingredient

Undecylenic Acid 25.00%

Purpose

Antifungal

Uses:

- For the cure of most tinea pedis (athlete's foot) and tinea corporis (ringworm).
- For effective relief of itching, scaling, cracking, burning, redness, soreness, irritation, discomfort associated to fungal infections.

Warnings:

For external use only

Do not use

- on children under 2 years of age unless directed by a doctor

When using this product

- Avoid contact with eyes.

Stop use and ask a doctor if

- If irritation occurs or if there is no improvement within 4 weeks, discontinue use and consult a doctor (within 2 weeks for jock itch).

Keep out of reach of children.

If swallowed, get medical help or contact a Poison Control Center right away.

If pregnant or breast-feeding,

ask a health professional before use.

Directions:

- Clean the affected area and dry thoroughly.
- Apply a thin layer of the product over affected area twice daily (morning and night) or as directed by a doctor.
- Supervise children in the use of this product.
- For arthlete's foot: Pay special attention to spaces between the toes; wear well-fitting, ventilated shoes, and change shoes and socks at least once daily.
- For athlete's foot and ringworm, use daily for 4 weeks.
- If condition persists longer, consult a doctor.
- This product is no effective on the scalp or nails.

Other Information:

- Protect the product in this container from excessive heat and direct sun.

Inactive Ingredients:

Aloe Extract, Eugenia Caryophyllus (Clove) Bud Oil, Helianthus Annuus (Sunflower) Oil, Malaleuca Alternifolia (Tea Tree) Oil, Menthol, Olea Europaea (Olive) Oil, Prunus Amygdalus Dulcis (Sweet Almond) Oil, Tocopheryl Acetate (Vitamin E).